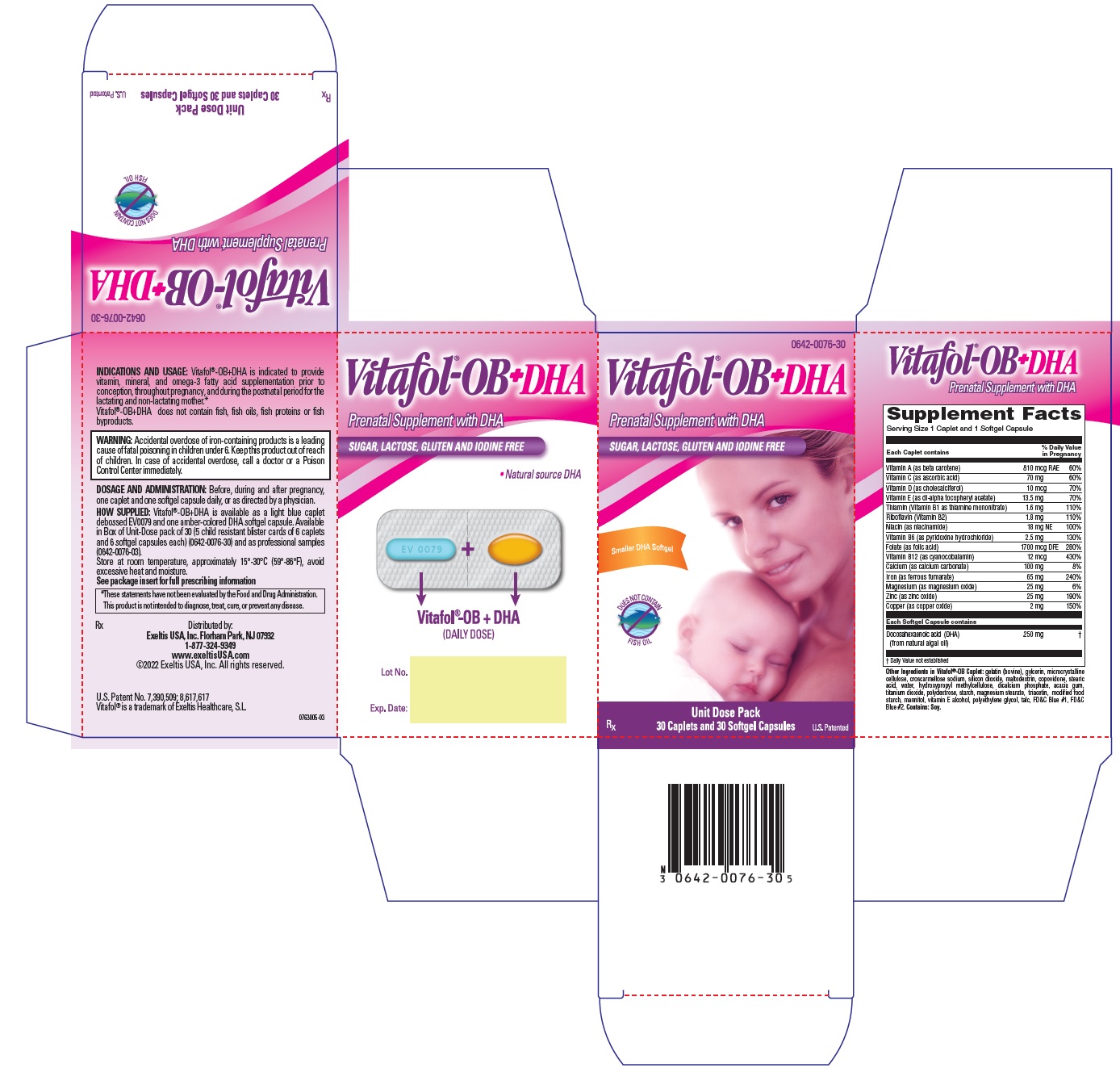 DRUG LABEL: Vitafol-OB Plus DHA
NDC: 0642-0076 | Form: KIT | Route: ORAL
Manufacturer: Exeltis USA, Inc
Category: prescription | Type: HUMAN PRESCRIPTION DRUG LABEL
Date: 20250320

ACTIVE INGREDIENTS: ASCORBIC ACID 70 mg/1 1; VITAMIN D 10 ug/1 1; .ALPHA.-TOCOPHEROL 13.5 mg/1 1; THIAMINE MONONITRATE 1.6 mg/1 1; RIBOFLAVIN 1.8 mg/1 1; NIACIN 18 mg/1 1; PYRIDOXINE HYDROCHLORIDE 2.5 mg/1 1; FOLIC ACID 1700 ug/1 1; CYANOCOBALAMIN 12 ug/1 1; CALCIUM 100 mg/1 1; IRON 65 mg/1 1; MAGNESIUM 25 mg/1 1; ZINC 25 mg/1 1; COPPER 2 mg/1 1; VITAMIN A 810 ug/1 1; DOCONEXENT 250 mg/1 1
INACTIVE INGREDIENTS: HYDROXYPROPYL METHYLCELLULOSE; COPOVIDONE K25-31; MANNITOL; POLYDEXTROSE; MALTODEXTRIN; SOYBEAN; MICROCRYSTALLINE CELLULOSE; STEARIC ACID; CROSCARMELLOSE SODIUM; ANHYDROUS DIBASIC CALCIUM PHOSPHATE; SILICON DIOXIDE; MODIFIED CORN STARCH (1-OCTENYL SUCCINIC ANHYDRIDE); STARCH, CORN; TOCOPHEROL; MAGNESIUM STEARATE; TITANIUM DIOXIDE; ACACIA; POLYETHYLENE GLYCOL, UNSPECIFIED; TRIACETIN; FD&C BLUE NO. 1; FD&C BLUE NO. 2; TALC; GLYCERIN; GELATIN, UNSPECIFIED; WATER

Vitafol®-OB+DHA

Prenatal Supplement with DHA

Rx

COMPOSITION

Each Vitafol®-OB caplet contains:

Vitamin A (as beta carotene) | 810 mcg RAE
Vitamin C (as ascorbic acid) | 70 mg
Vitamin D (as cholecalciferol) | 10 mcg
Vitamin E (as dl-alpha tocopheryl acetate) | 13.5 mg
Thiamin (Vitamin B1 as thiamine mononitrate) | 1.6 mg
Riboflavin (Vitamin B2) | 1.8 mg
Niacin (as niacinamide) | 18 mg NE
Vitamin B6 (as pyridoxine hydrochloride) | 2.5 mg
Folate (as folic acid) | 1700 mcg DFE
Vitamin B12 (as cyanocobalamin) | 12 mcg
Calcium (as calcium carbonate) | 100 mg
Iron (as ferrous fumarate) | 65 mg
Magnesium (as magnesium oxide) | 25 mg
Zinc (as zinc oxide) | 25 mg
Copper (as copper oxide) | 2 mg
Each DHA softgel capsule contains:
Docosahexaenoic acid (DHA); (from natural algal oil) | 250 mg

Other ingredients: gelatin (bovine), gylcerin, microcrystalline cellulose, croscarmellose sodium, silicon dioxide, maltodextrin, copovidone, stearic acid, water, hydroxypropyl methylcellulose, dicalcium phosphate, acacia gum, titanium dioxide, polydextrose, starch, magnesium stearate, triacetin, modified food starch, mannitol, vitamin E alcohol, polyethylene glycol, talc, FD&C Blue #1, FD&C Blue #2. Contains: Soy.

INDICATIONS AND USAGE

Vitafol®-OB+DHA is indicated to provide vitamin, mineral and omega-3 fatty acid supplementation prior to conception, throughout pregnancy, and during the postnatal period for the lactating and non-lactating mother.*

Vitafol®-OB+DHA does not contain fish, fish oils, fish proteins or fish byproducts.

CONTRAINDICATIONS

Vitafol®-OB+DHA is contraindicated in patients with hypersensitivity to any of its components or color additives.

Folic acid is contraindicated in patients with untreated and uncomplicated pernicious anemia, and in those with anaphylactic sensitivity to folic acid.

Iron therapy is contraindicated in patients with hemochromatosis and patients with iron storage disease or the potential for iron storage disease due to chronic hemolytic anemia (e.g., inherited anomalies of hemoglobin structure or synthesis and/or red cell enzyme deficiencies, etc.), pyridoxine responsive anemia, or cirrhosis of the liver.

Cyanocobalamin is contraindicated in patients with sensitivity to cobalt or to cyanocobalamin (vitamin B-12).

Warning

Accidental overdose of iron-containing products is a leading cause of fatal poisoning in children under 6. Keep this product out of reach of children. In case of accidental overdose, call a doctor or a Poison Control Center immediately.

WARNINGS/PRECAUTIONS

Vitamin D supplementation should be used with caution in those with hypercalcemia or conditions that may lead to hypercalcemia such as hyperparathryroidism and those who form calcium-containing kidney stones. High doses of vitamin D can lead to elevated levels of calcium that reside in the blood and soft tissues. Bone pain, high blood pressure, formation of kidney stones, renal failure, and increased risk of heart disease can occur.

Prolonged use of iron salts may produce iron storage disease.

Folic acid, especially in doses above 0.1 mg daily, may obscure pernicious anemia, in that hematologic remission may occur while neurological manifestations remain progressive.

The use of folic acid doses above 1 mg daily may precipitate or exacerbate the neurological damage of vitamin B12 deficiency. Consumption of more than 3 grams of omega-3 fatty acids per day from all sources may lead to excessive bleeding.

Supplemental intake of omega-3 fatty acids, such as DHA exceeding 2 grams per day is not recommended.

Avoid overdosage. Keep out of the reach of children.

Drug Interactions

High doses of folic acid may result in decreased serum levels of the anticonvulsant drugs.

Vitamin D supplementation should not be given with large amounts of calcium in those with hypercalcemia or conditions that may lead to hypercalcemia such as hyperparathyroidism and those who form calcium-containing kidney stones.

Zinc can inhibit the absorption of certain antibiotics; take at least 2 hours apart to minimize interactions.

Consult appropriate references for additional specific vitamin-drug interactions.

Information for Patients

Patients should be counseled to disclose all medical conditions, including use of all medications, vitamins and supplements, pregnancy, and breast-feeding.

Pediatric Use

Not for pediatric use.

ADVERSE REACTIONS

Adverse reactions have been reported with specific vitamins and minerals, but generally at doses substantially higher than those in Vitafol®-OB+DHA. Allergic reactions have been reported with some forms of gum acacia to include respiratory problems and skin lesions.

Contact your doctor for medical advice about serious adverse events. To report a serious adverse event or obtain
product information, contact 1-877-324-9349.

DOSAGE AND ADMINISTRATION

Before, during and after pregnancy, take one caplet and one soft-gel capsule by mouth daily, or as directed by a physician.

HOW SUPPLIED

Vitafol®-OB+DHA is available as a light blue caplet debossed EV0079 and one amber-colored DHA softgel capsule. Available in Box of Unit-Dose pack of 30 (5 child resistant blister cards of 6 caplets and 6 softgel capsules each) (0642-0076-30) and as professional samples (0642-0076-03).

STORAGE AND HANDLING

Store at room temperature, approximately 15°-30°C (59°-86°F), avoid excessive heat and moisture.

*These statements have not been evaluated by the Food and Drug Administration. This product is not intended to diagnose, treat, cure, or prevent any disease.

Rx

Distributed by:
Exeltis USA, Inc.
Florham Park, NJ 07932
1-877-324-9349
www.exeltisusa.com
©2024 Exeltis USA, Inc.

U.S. Patent No. 6,814,983; 7,390,509
Vitafol® is a trademark of Exeltis USA, Inc.

Rev. July 2024

0763001-04

PRINCIPAL DISPLAY PANEL - Kit Carton

0642-0076-30

Vitafol®-OB+DHA

Prenatal Supplement with DHA

SUGAR, LACTOSE, GLUTEN AND IODINE FREE

New
Smaller DHA Softgel

DOES NOT CONTAIN
FISH OIL

RX
Unit Dose Pack
30 Caplets and 30 Softgel Capsules
U.S. Patented